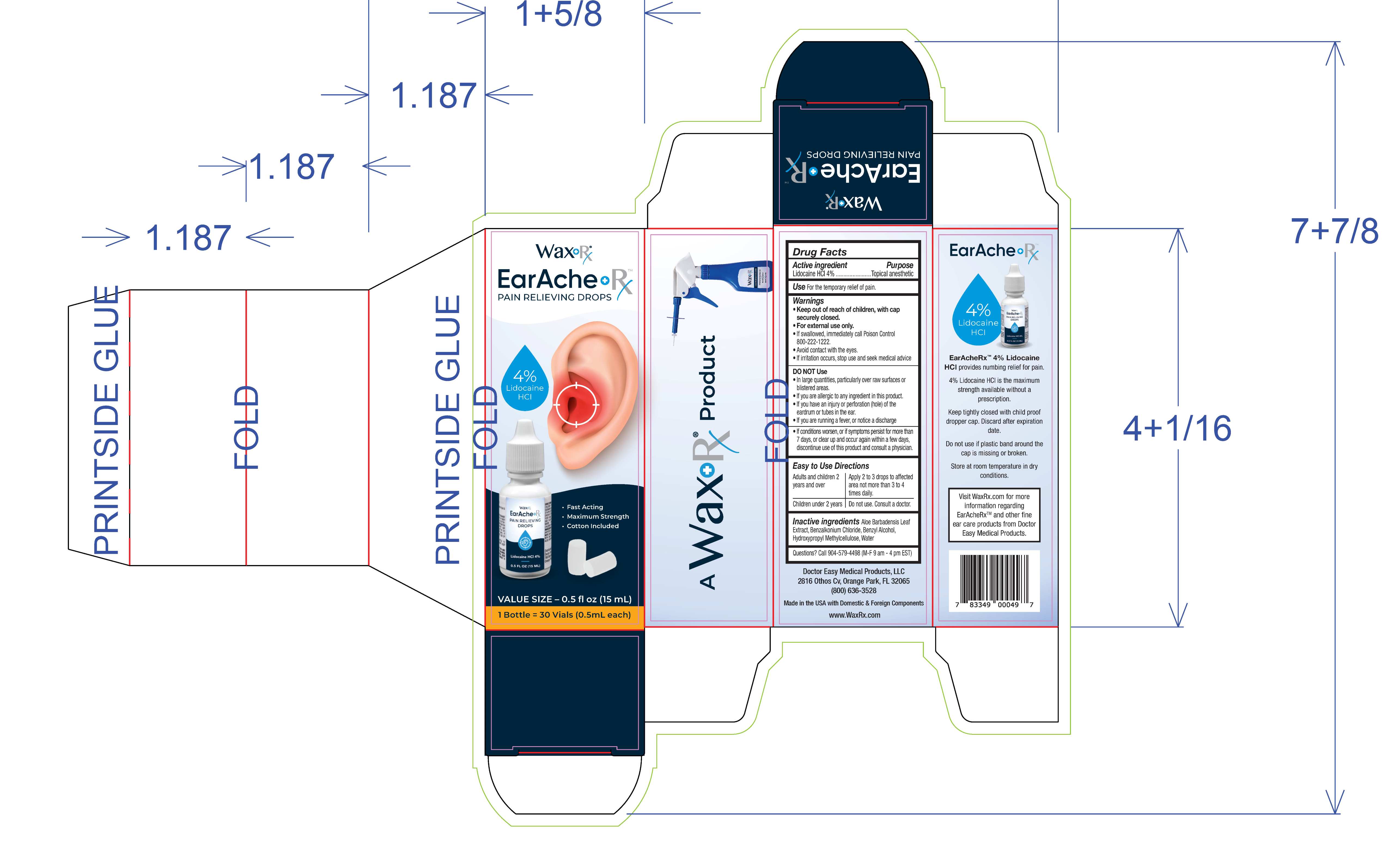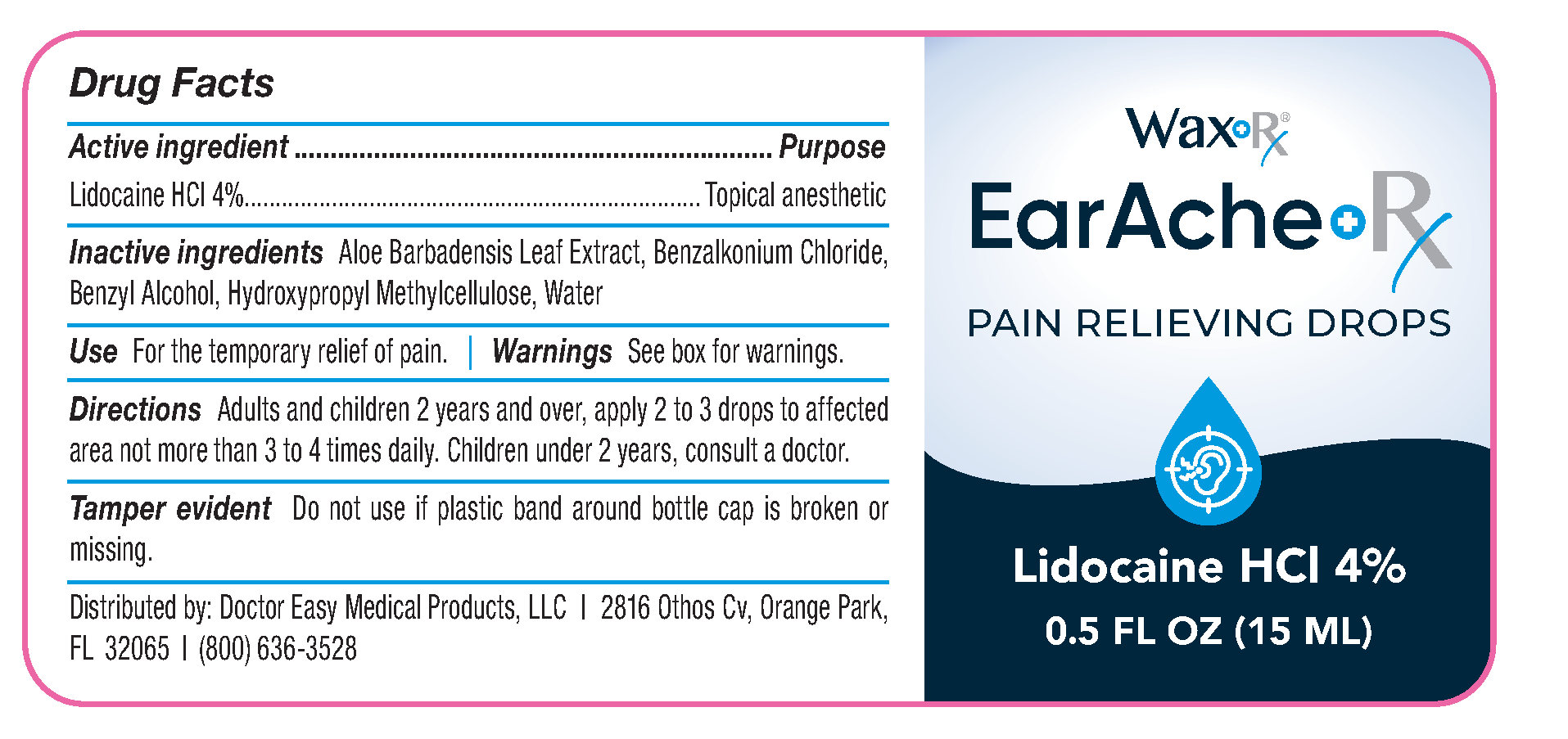 DRUG LABEL: WaxRx EarAcheRx Pain Relieving Drops
NDC: 72724-002 | Form: LIQUID
Manufacturer: DOCTOR EASY MEDICAL PRODUCTS, LLC
Category: otc | Type: HUMAN OTC DRUG LABEL
Date: 20250501

ACTIVE INGREDIENTS: LIDOCAINE HYDROCHLORIDE ANHYDROUS 4 g/100 mL
INACTIVE INGREDIENTS: HYDROXYPROPYL METHYLCELLULOSE; ALOE BARBADENSIS LEAF; BENZALKONIUM CHLORIDE; WATER; BENZYL ALCOHOL

ACTIVE INGREDIENT

Lidocaine HCL 4%

PURPOSE

Lidocaine HCL 4%...................Topical Anesthetic

INDICATIONS AND USAGE

For the temporary relief of pain.

- Keep out of reach of children, with cap securely closed.
- For external use only.
- If swallowed, immediately call Poison Control 800-222-1222
- Avoid contact with the eyes.
- If irritation occurs, stop and seek medical advice

DO NOT Use

- In large quantities, particularly over raw surfaces or blistered areas.
- If you are allergic to any ingredient in this product.
- If you have an injury or perforation (hole) of the eardrum or tubes in the ear.
- If you are running a fever, or notice a discharge.
- If conditions worsen, or if symptoms persist for more than 7 days, or clear up and occur again within a few days, discontinue use of this product and consult a physician.

Keep out of reach of children, with cap securely closed.
If swallowed, immediately call Poison Control 800-222-1222

Easy to Use Directions

Adults and children 2 years and over

Apply 2 to 3 drops to affected area not more than 3 to 4 times daily.
Children under 2 years Consult a doctor.

INACTIVE INGREDIENT

Aloe Barbadensis Leaf Extract, Benzalkonium Chloride, Benzyl Alcohol, Hydroxypropyl Methycellulose, Water

PACKAGE LABEL

WaxRx

EarAcheRx

Pain Relieving Drops

4% Lidocaine HC

0.5 FL OZ (15 ML)